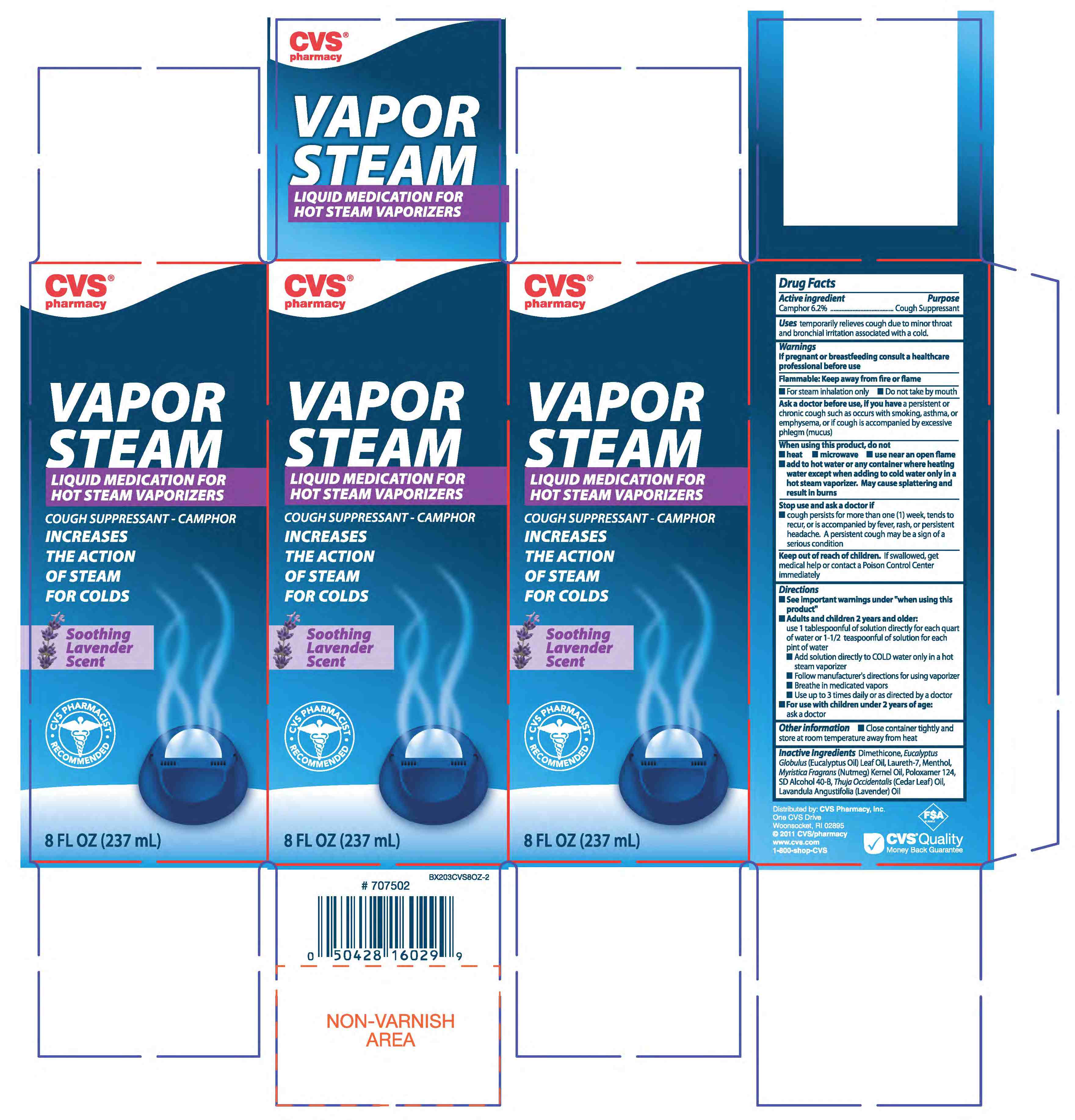 DRUG LABEL: CAMPHOR
NDC: 59779-058 | Form: LIQUID
Manufacturer: CVS
Category: otc | Type: HUMAN OTC DRUG LABEL
Date: 20110216

ACTIVE INGREDIENTS: CAMPHOR (SYNTHETIC) 155 mg/1 mL
INACTIVE INGREDIENTS: ALCOHOL; CEDRUS ATLANTICA BARK; EUCALYPTUS OIL; LAURETH-7; MENTHOL; NUTMEG OIL; POLOXAMER 124; CYCLOMETHICONE 5; ENGLISH LAVENDER OIL

drug facts

Active ingredient Purpose
Camphor 6.2%.............................Cough Suppressant

Active ingredient Purpose
Camphor 6.2%..................Cough Suppressant
______________________________________
Uses temporarily relieves cough due to minor throat
and bronchial irritation associated with a cold.

Keep out of reach of children. If swallowed, get
medical help or contact a Poison Control Center immediately.

INDICATIONS AND USAGE

Uses - temporarily relieves cough due to minor throat
and bronchial irritation associated with a cold.

Warnings
If pregnant or breastfeeding consult a healthcare
professional before use
___________________________________________________
Flammable Keep away from fire or flame
_____________________________________________
- for steam inhalation only - do not take by mouth
____________________________________________________
Ask a doctor before use if you have a persistent or
chronic cough such as occurs with smoking, asthma, or
emphysema, or if cough is accompanied by excessive
phlegm (mucus)
_____________________________________________________
When using this product do not
- heat - microwave - use near an open flame
- add to hot water or any container where heating
water except when adding to cold water only in a
hot steam vaporizer. May cause splattering and
result in burns
______________________________________________________
Stop use and ask a doctor if
-cough persists for more than one (1) week, tends to
recur, or is accompanied by fever, rash or persistent
headache. A persistent cough may be a sign of a
serious condition
______________________________________________________
Keep out of reach of children. If swallowed, get
medical help or contact a Poison Control Center
immediately
______________________________________________________

Directions
- See Important warnings under "When using this
product"
- Adults and children 2 years and older:
use 1 tablespoon of solution directly for each quart
of water or 1-1/2 teaspoonful of solution for each
pint of water
- add solution directly to COLD water only in a hot
steam vaporizer
- follow manufacturer's directions for using vaporizer
- Breath in medicated vapors
- use up to 3 times daily or as directed by a doctor
- For use with children under 2 years of age:
ask a doctor
________________________________
Other information - Close container tightly and
store at room temperature away from heat

Inactive Ingredients Dimethicone, Eucalyptus
Globulus (Encalyptus Oil) Leaf Oil, Laureth-7, Menthol,
Mys=ristica Fragrans (nutmeg) Kernal Oil, Poloxarner 124,
SD Alcohol 40-B, Thuja Occidentalis (Cedar Leaf) Oil,
Lavandula Angustifolia (Lavender) Oil